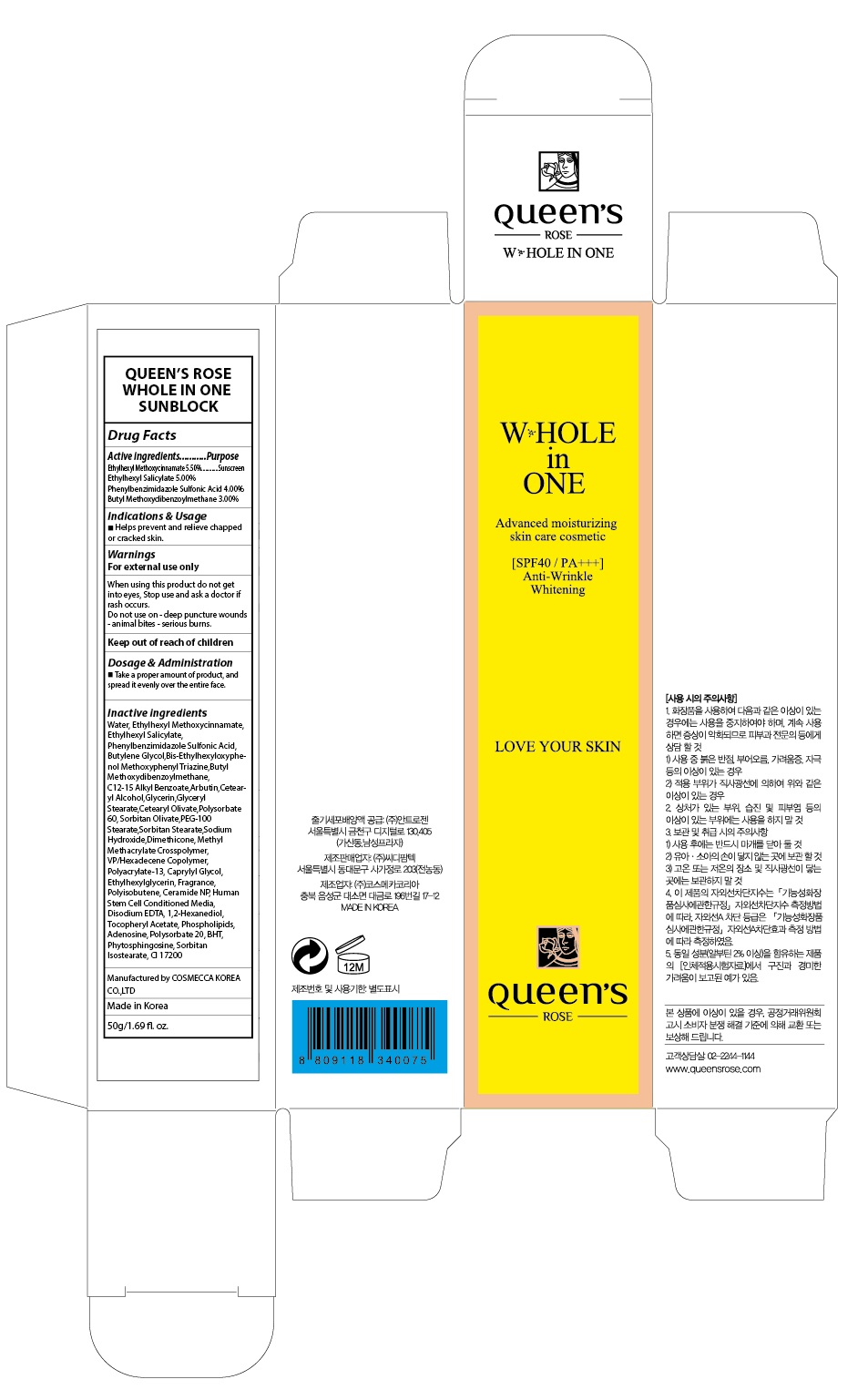 DRUG LABEL: QUEENS ROSE WHOLE IN ONE SUNBLOCK
NDC: 71252-100 | Form: CREAM
Manufacturer: Cdpharmtec Co.,ltd
Category: otc | Type: HUMAN OTC DRUG LABEL
Date: 20170324

ACTIVE INGREDIENTS: OCTINOXATE 2.75 g/50 g; OCTISALATE 2.5 g/50 g; ENSULIZOLE 2.0 g/50 g; AVOBENZONE 1.5 g/50 g
INACTIVE INGREDIENTS: Water; Butylene Glycol

ACTIVE INGREDIENT

Active ingredients: Ethylhexyl Methoxycinnamate 5.50%, Ethylhexyl Salicylate 5.00%, Phenylbenzimidazole Sulfonic Acid 4.00%, Butyl Methoxydibenzoylmethane 3.00%

INACTIVE INGREDIENT

Inactive ingredients: Water, Butylene Glycol,Bis-Ethylhexyloxyphenol Methoxyphenyl Triazine, C12-15 Alkyl Benzoate,Arbutin,Cetearyl Alcohol,Glycerin,Glyceryl Stearate,Cetearyl Olivate,Polysorbate 60, Sorbitan Olivate,PEG-100 Stearate,Sorbitan Stearate,Sodium Hydroxide,Dimethicone, Methyl Methacrylate Crosspolymer, VP/Hexadecene Copolymer, Polyacrylate-13, Caprylyl Glycol, Ethylhexylglycerin, Fragrance, Polyisobutene, Ceramide NP, Human Stem Cell Conditioned Media, Disodium EDTA, 1,2-Hexanediol, Tocopheryl Acetate, Phospholipids, Adenosine, Polysorbate 20, BHT, Phytosphingosine, Sorbitan Isostearate, CI 17200

PURPOSE

Purpose: Sunscreen

WARNINGS

Warnings: For external use only When using this product do not get into eyes, Stop use and ask a doctor if rash occurs. Do not use on - deep puncture wounds - animal bites - serious burns.

Keep out of reach of children

DESCRIPTION

Indications & Usage: Helps prevent and relieve chapped or cracked skin.

Dosage & Administration: Take a proper amount of product, and spread it evenly over the entire face.